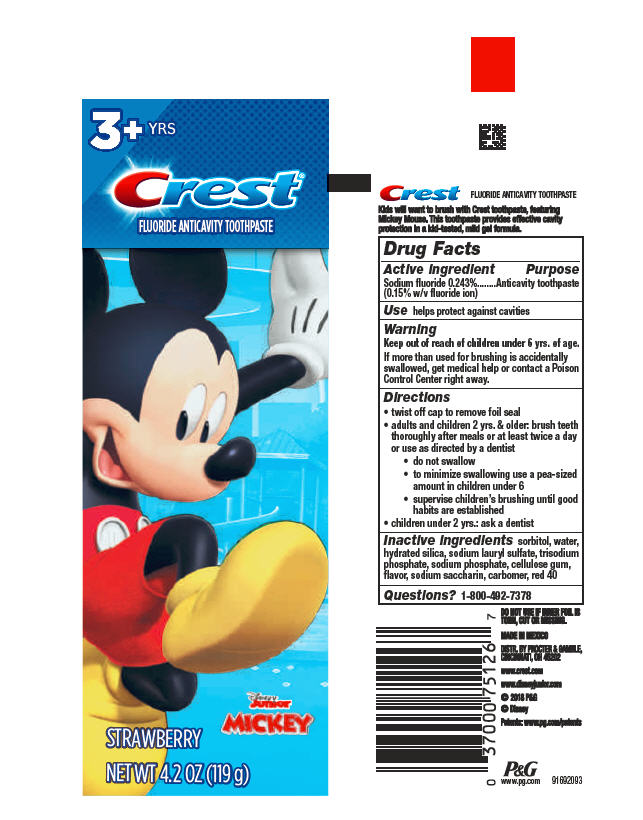 DRUG LABEL: Crest
NDC: 37000-171 | Form: PASTE, DENTIFRICE
Manufacturer: The Procter & Gamble Manufacturing Company
Category: otc | Type: HUMAN OTC DRUG LABEL
Date: 20260129

ACTIVE INGREDIENTS: SODIUM FLUORIDE 1.5 mg/1 g
INACTIVE INGREDIENTS: CARBOXYPOLYMETHYLENE; SACCHARIN SODIUM; SORBITOL; WATER; HYDRATED SILICA; SODIUM LAURYL SULFATE; SODIUM PHOSPHATE; CARBOXYMETHYLCELLULOSE SODIUM; SODIUM PHOSPHATE, TRIBASIC, ANHYDROUS; FD&C RED NO. 40

Crest®
Strawberry

Drug Facts

Active ingredient

Sodium fluoride 0.243% (0.15% w/v fluoride ion)

Purpose

Anticavity toothpaste

Use

helps protect against cavities

Warnings

Keep out of reach of children under 6 yrs. of age.

WHEN USING

If more than used for brushing is accidentally swallowed, get medical help or contact a Poison Control Center right away.

Directions

- twist off cap to remove foil seal
- adults and children 2 yrs. & older: brush teeth thoroughly after meals or at least twice a day or use as directed by a dentist
  - do not swallow
  - to minimize swallowing use a pea-sized amount in children under 6
  - supervise children's brushing until good habits are established
- children under 2 yrs.: ask a dentist

Inactive ingredients

sorbitol, water, hydrated silica, sodium lauryl sulfate, trisodium phosphate, sodium phosphate, cellulose gum, flavor, sodium saccharin, carbomer, red 40

Questions?

1-800-492-7378

MADE IN MEXICO
DISTR. BY PROCTER & GAMBLE,
CINCINNATI, OH 45202

PRINCIPAL DISPLAY PANEL - 119 g Tube

3+ YRS
Crest®

FLUORIDE ANTICAVITY TOOTHPASTE

Disney

Junior

MICKEY

STRAWBERRY

NET WT 4.2 OZ (119 g)